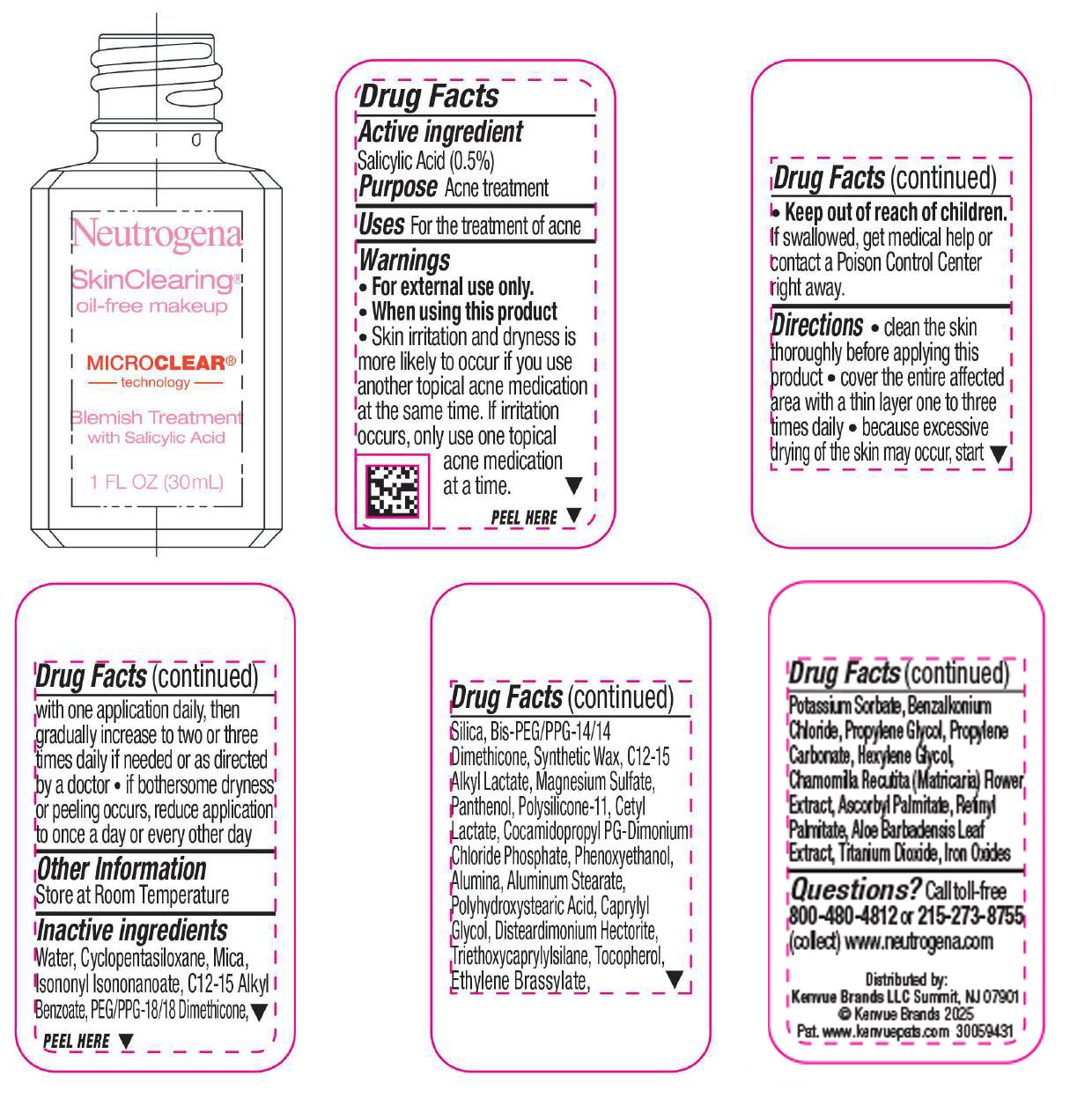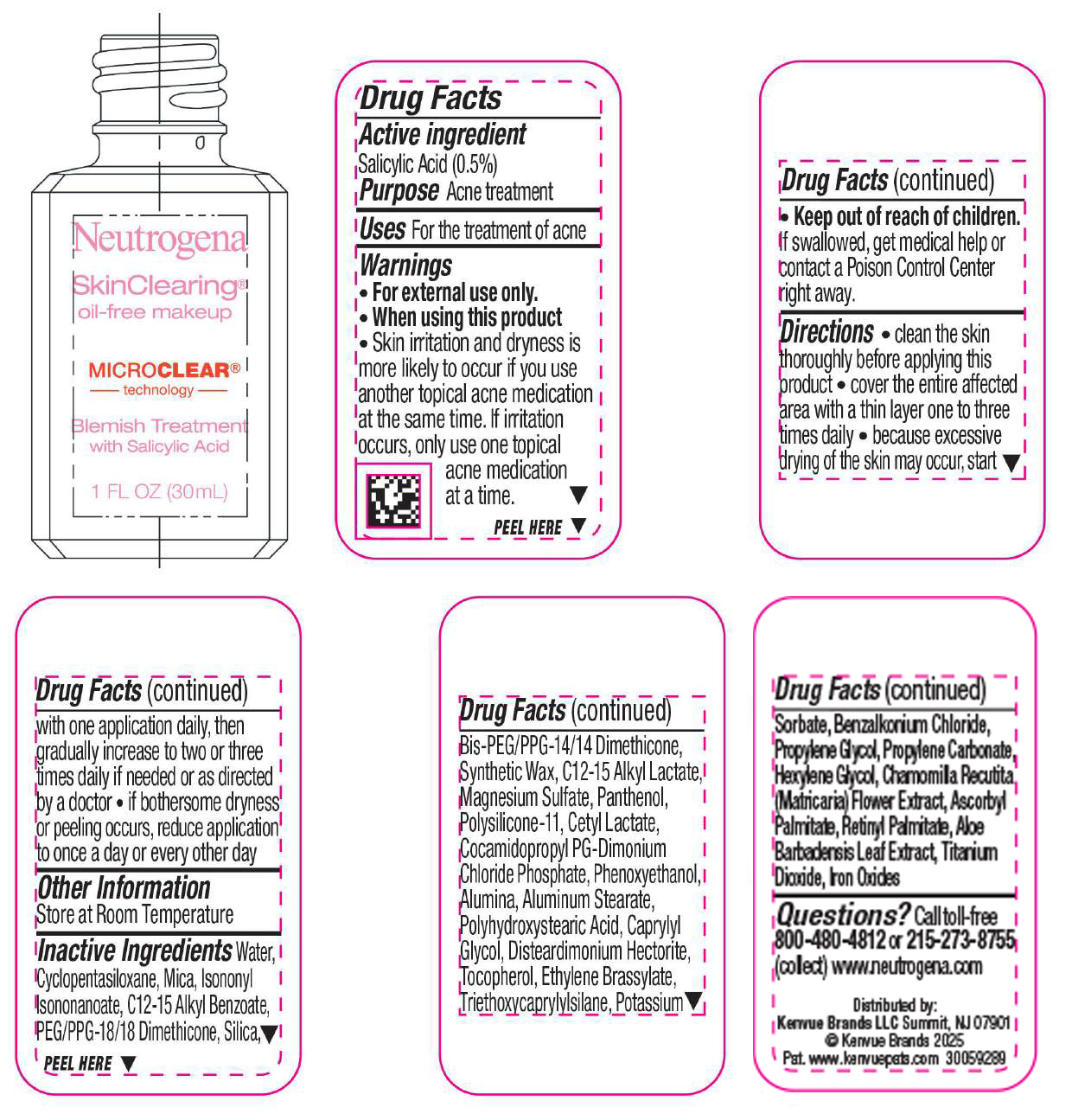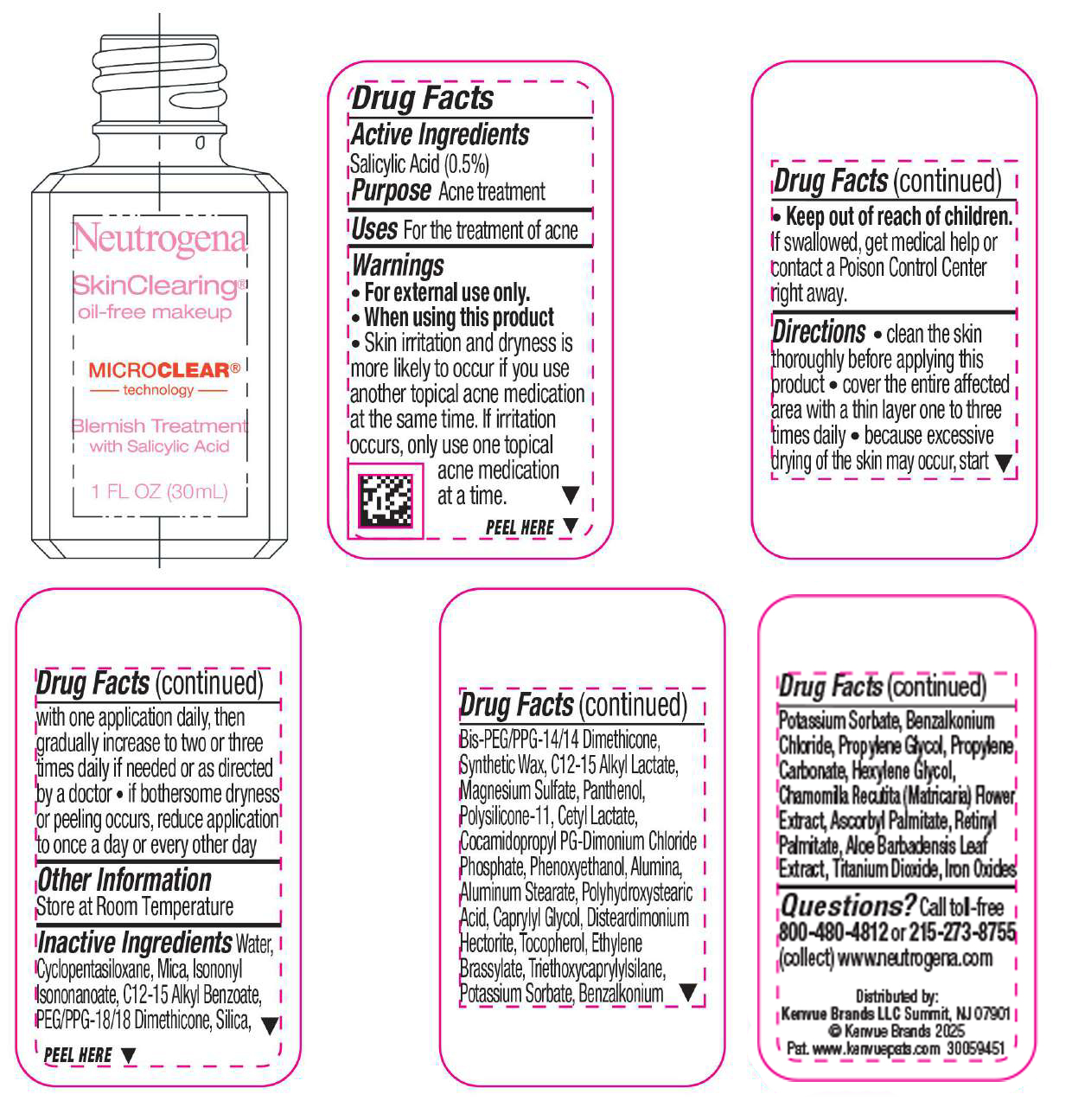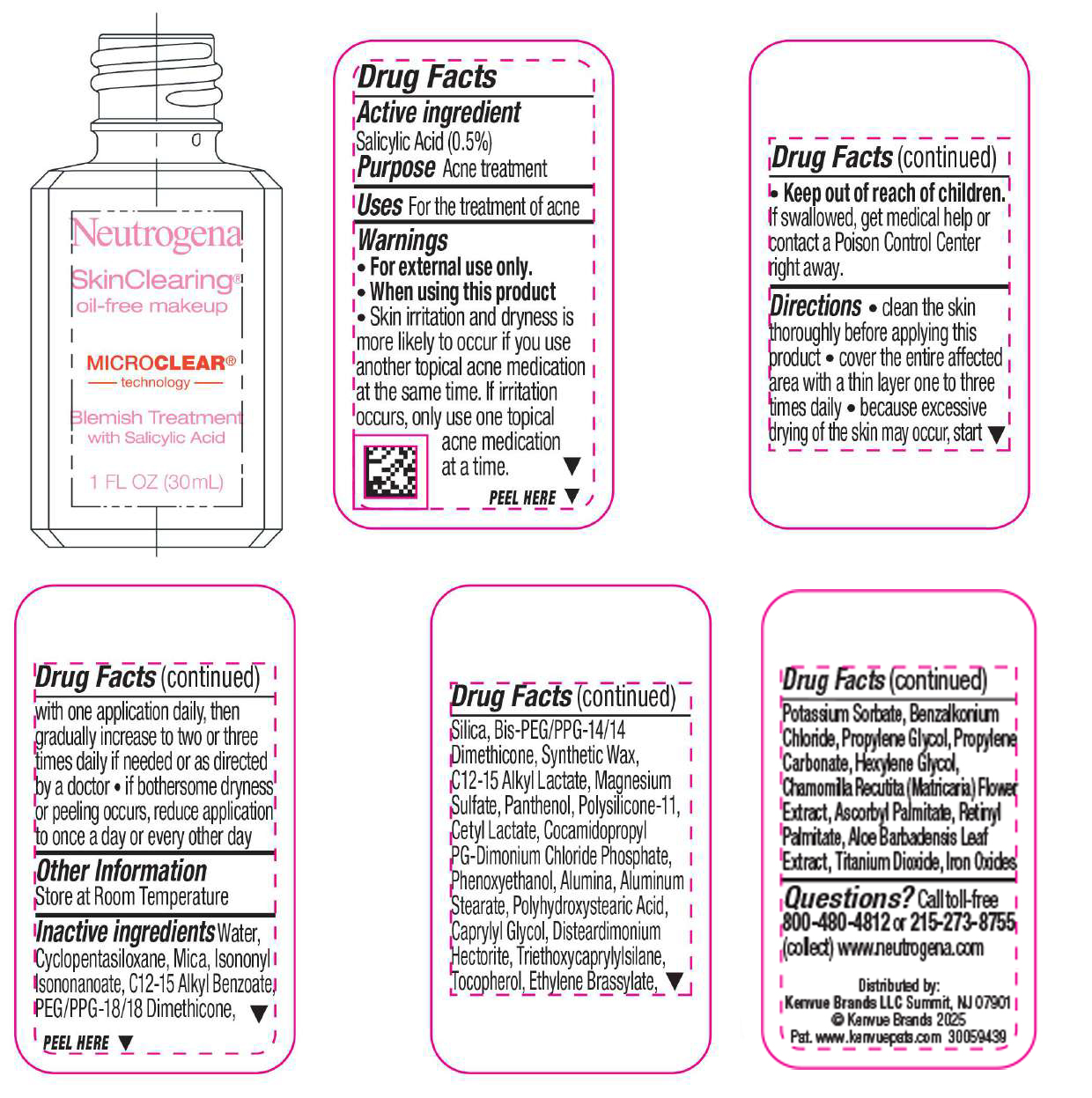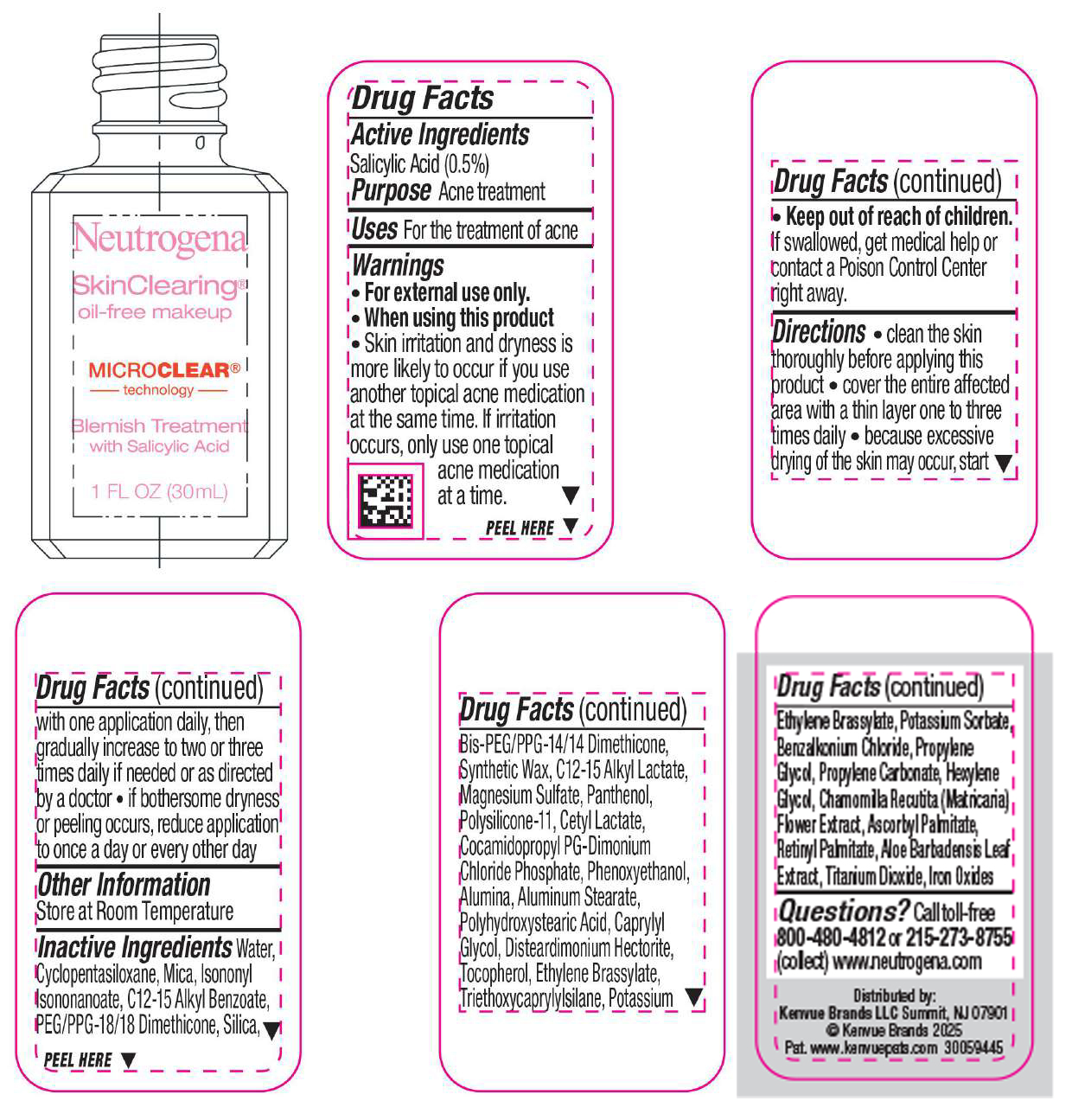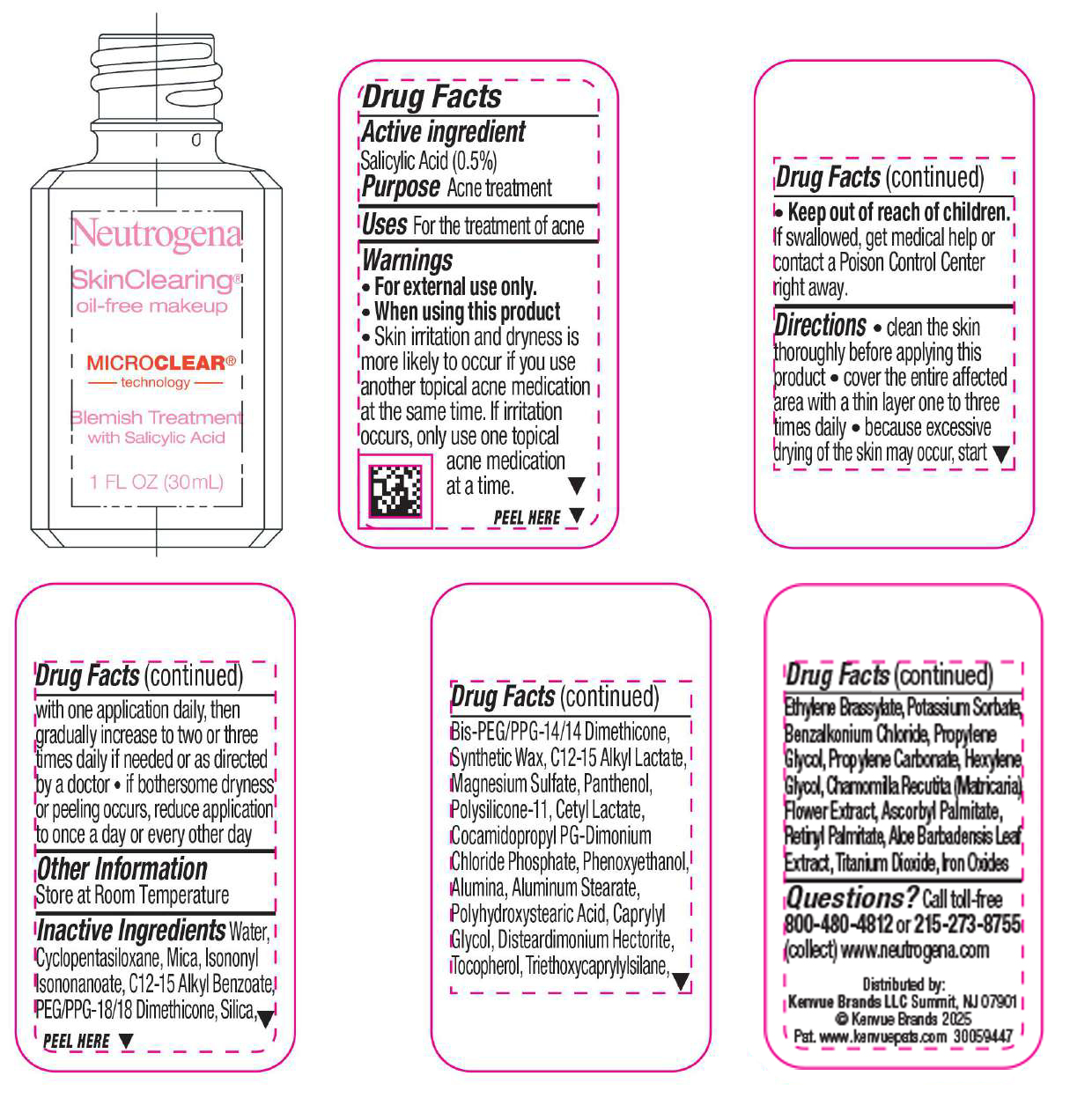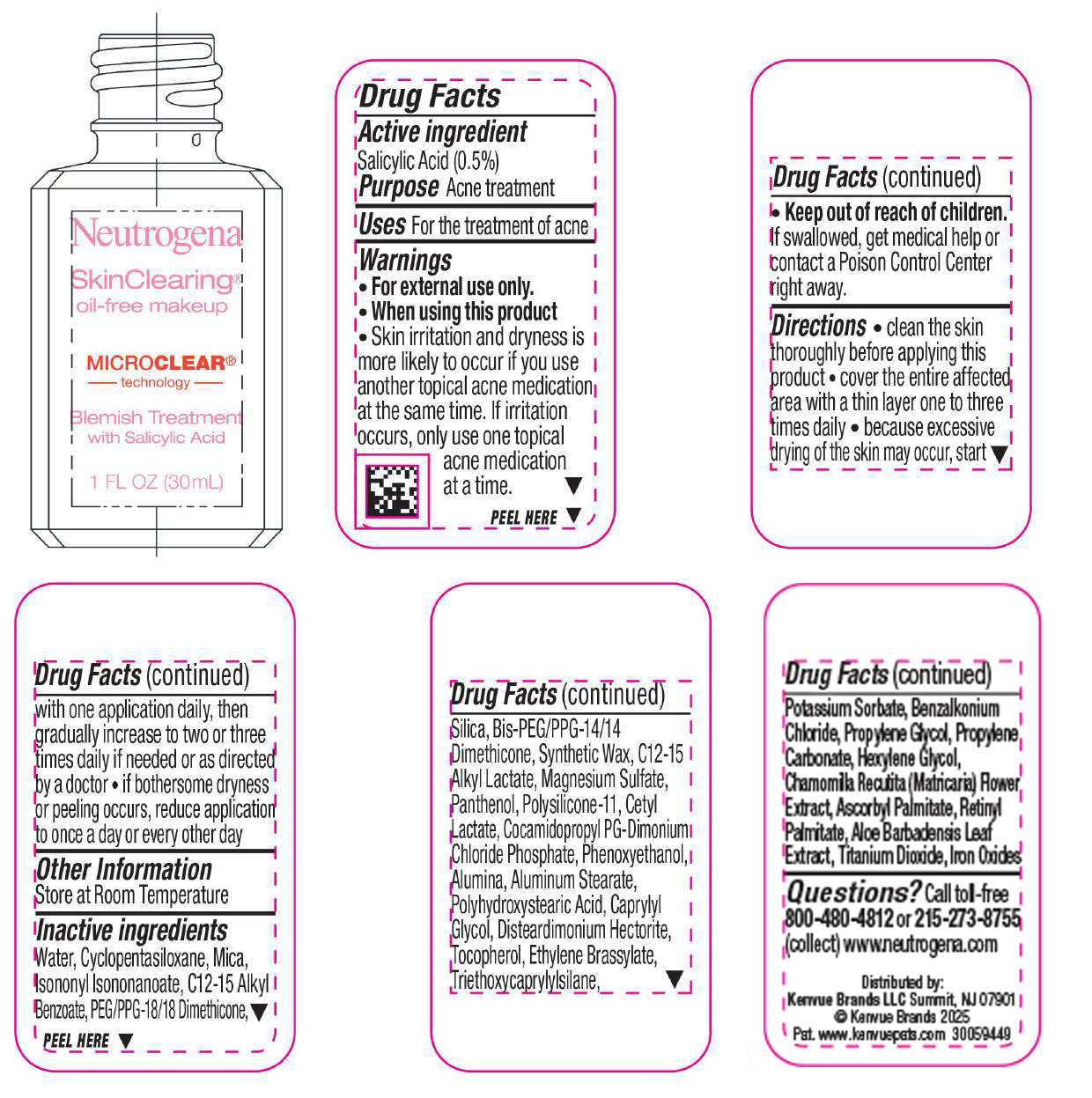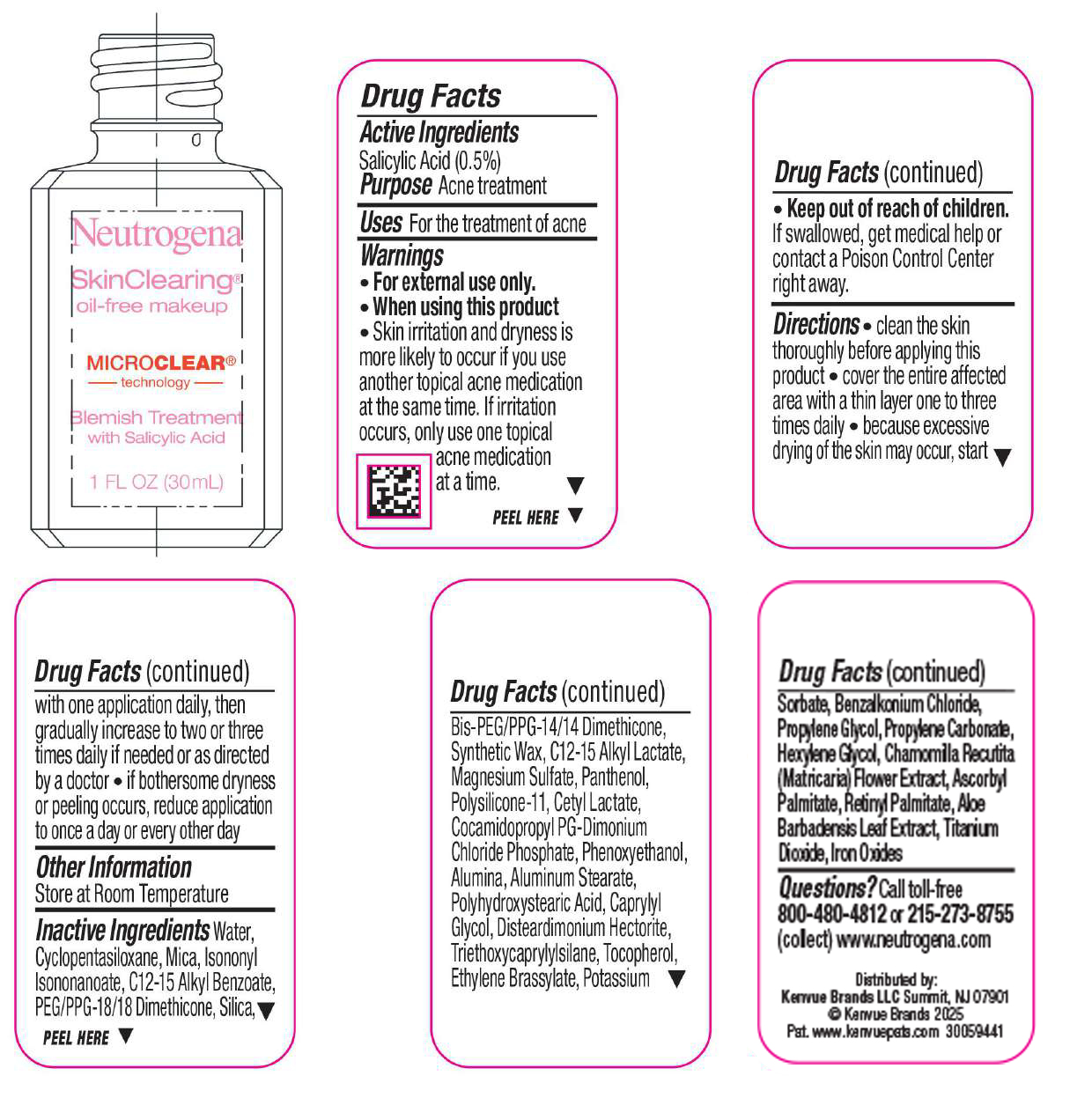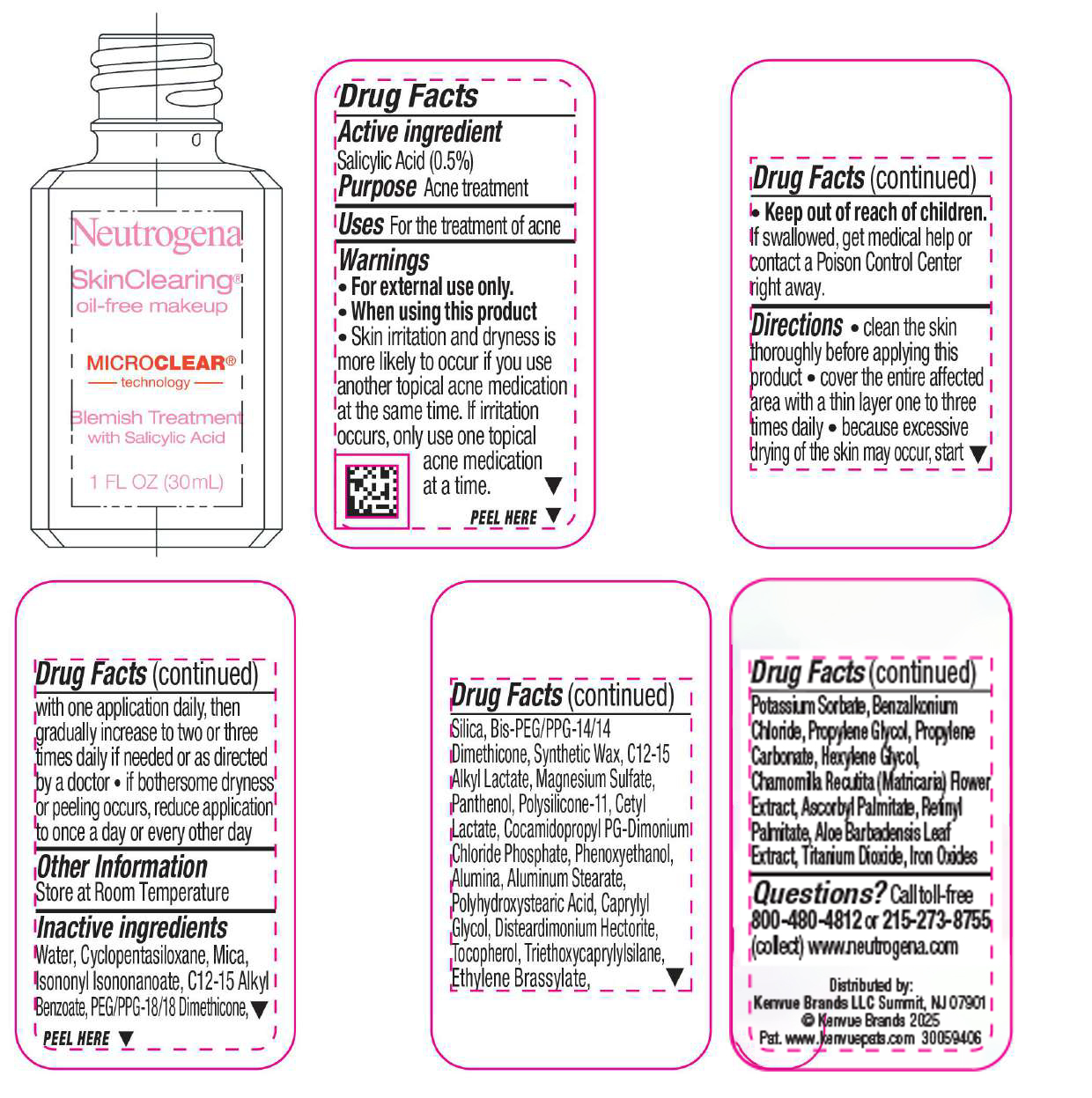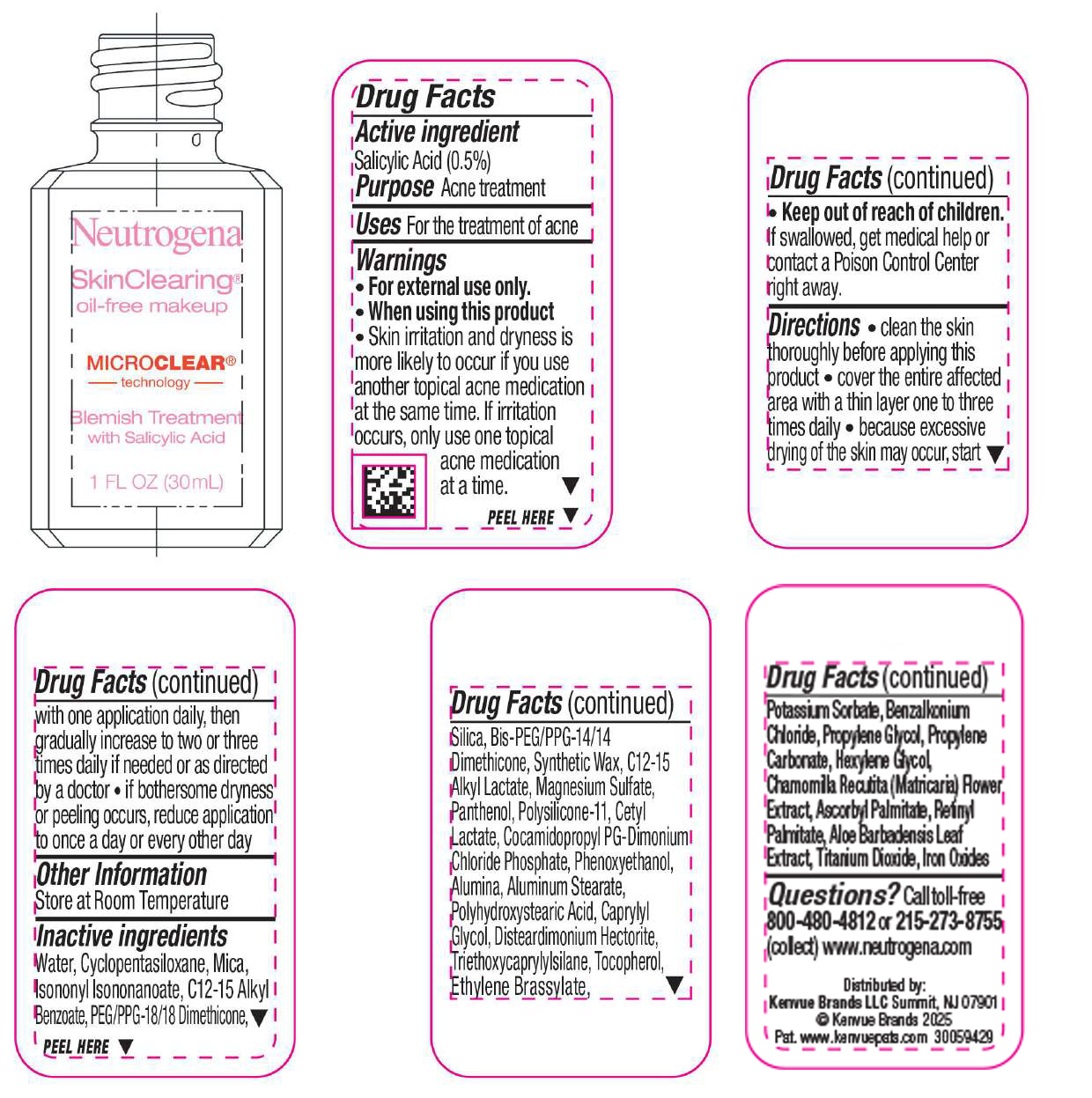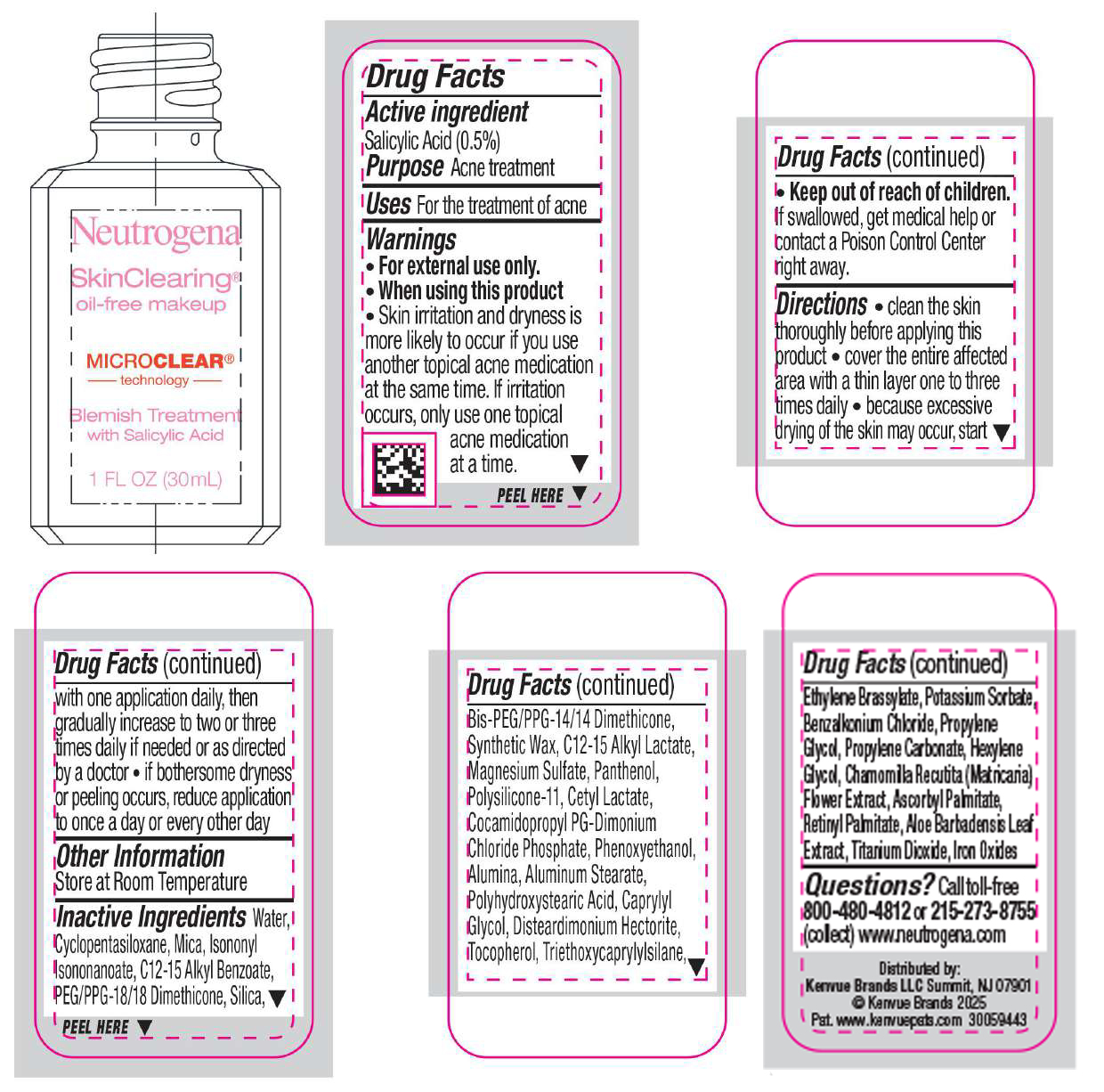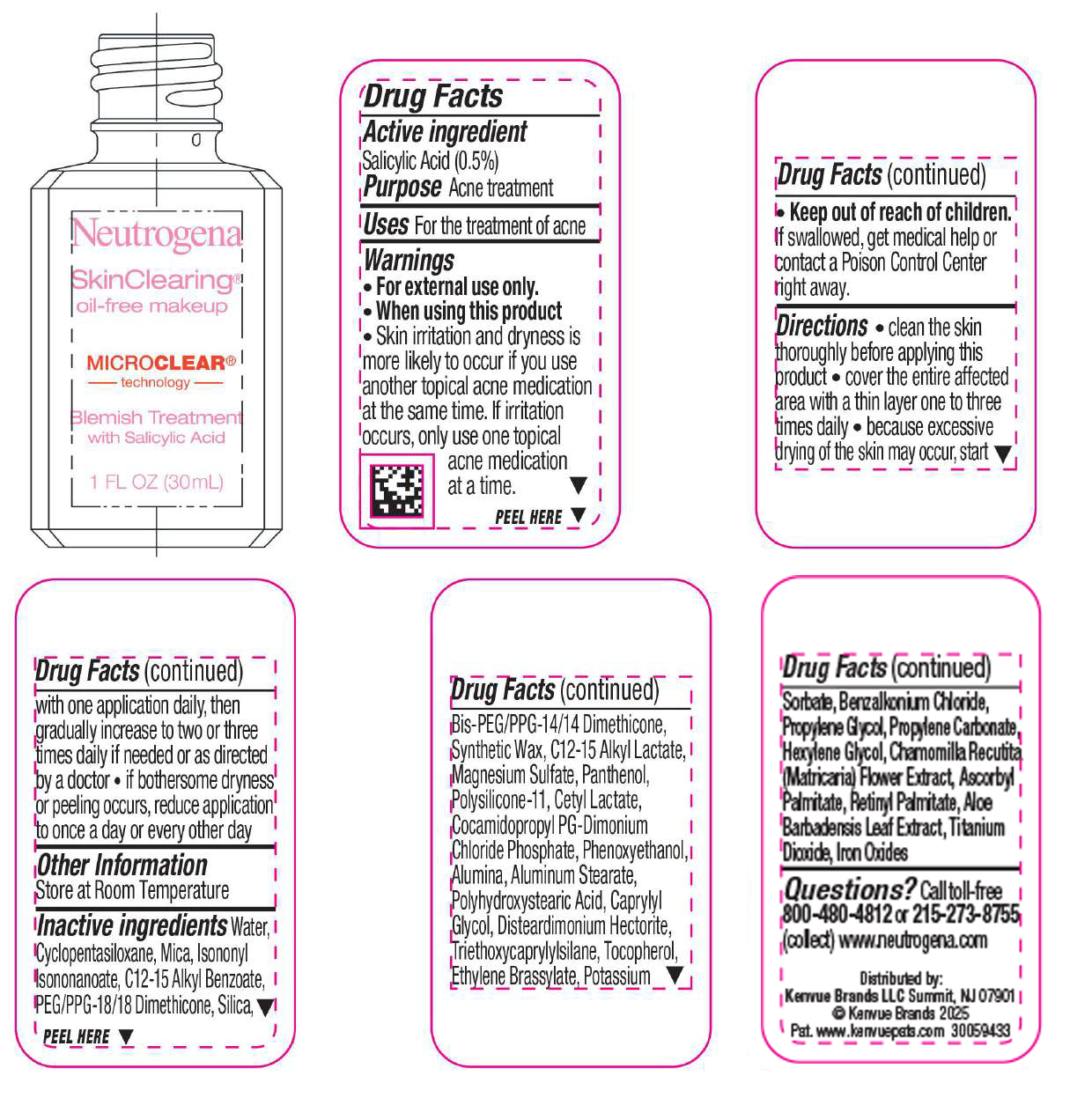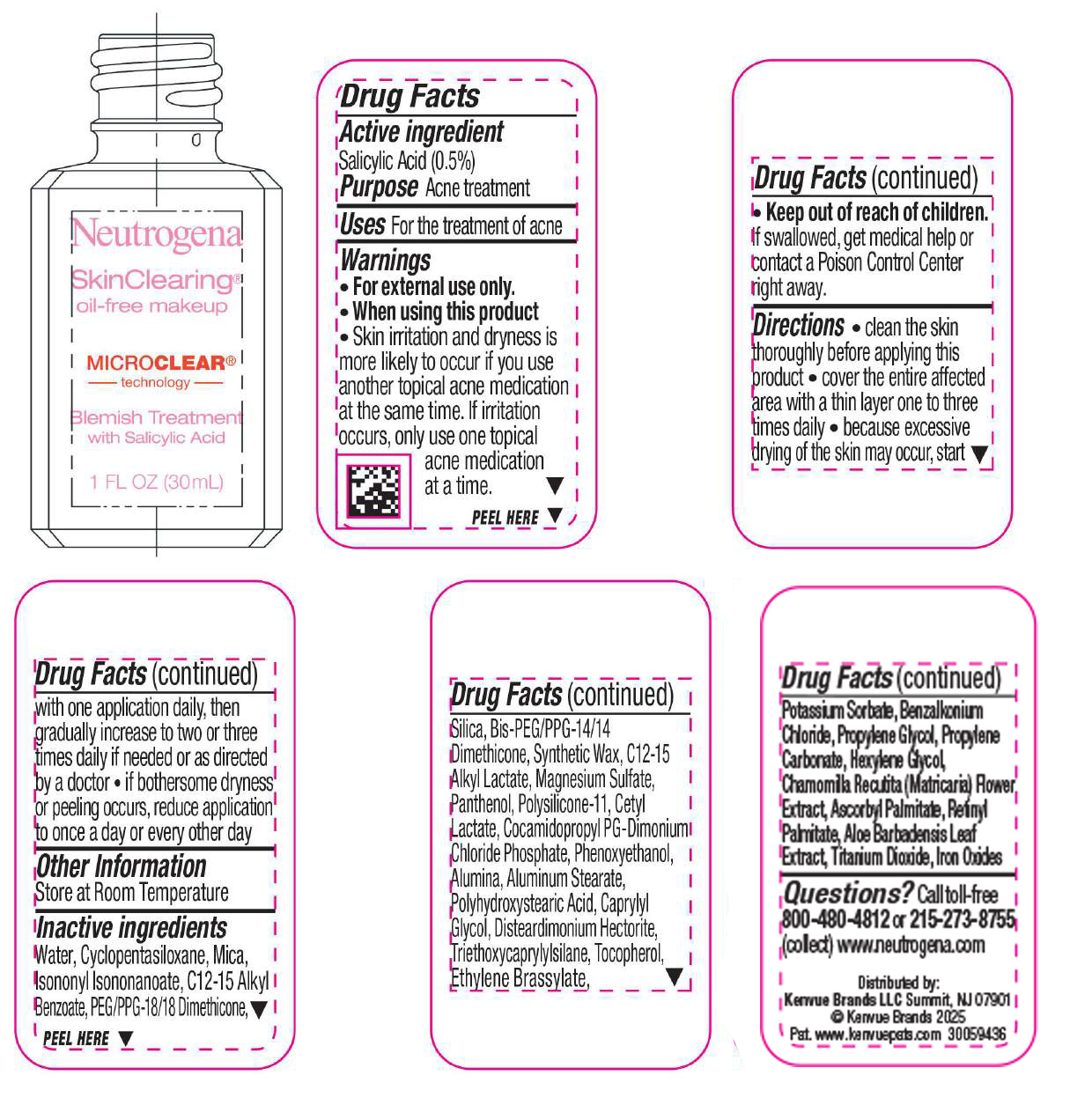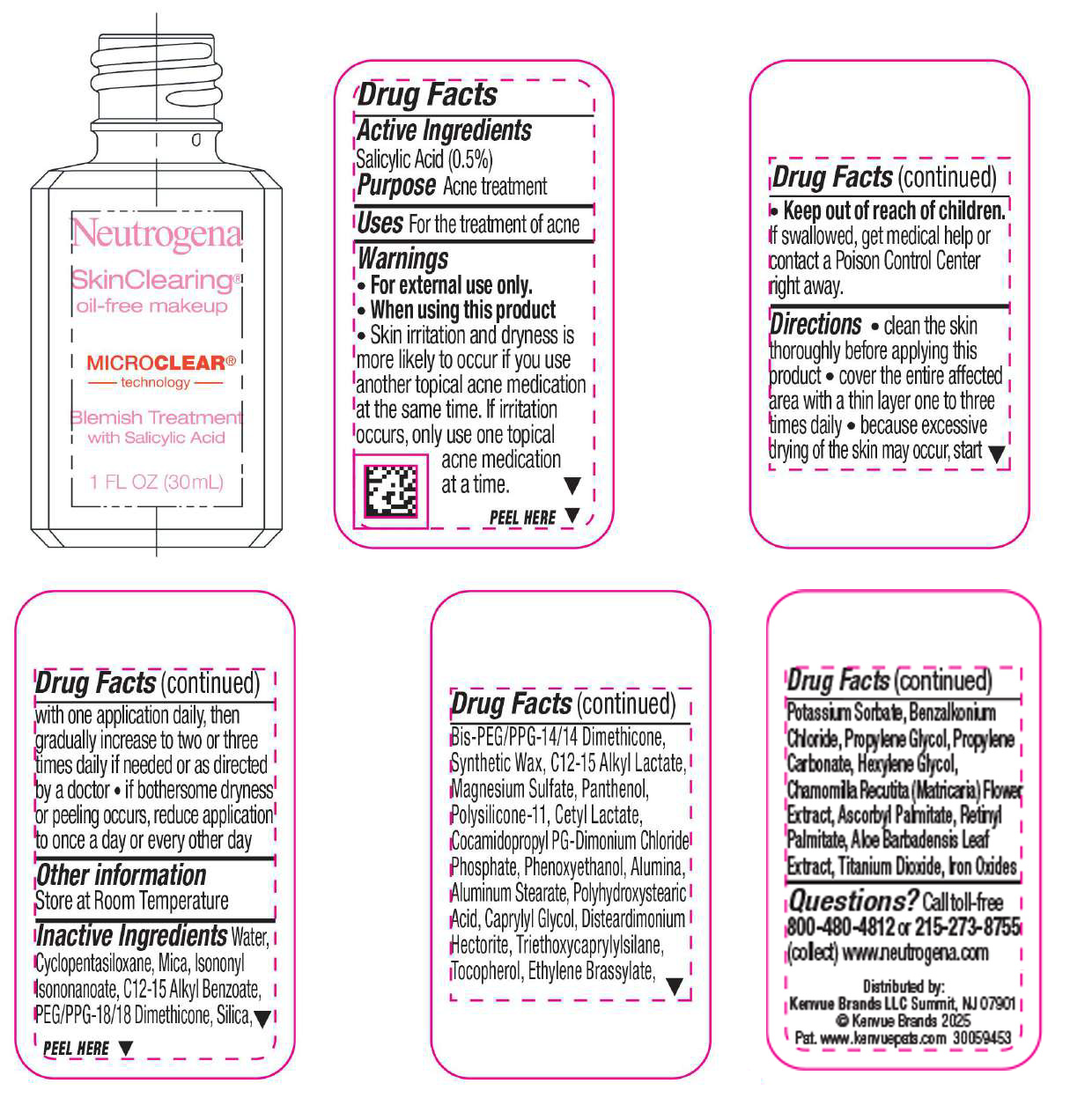 DRUG LABEL: Neutrogena SkinClearing Oil-Free Makeup - Soft Beige 50
NDC: 69968-0857 | Form: LIQUID
Manufacturer: Kenvue Brands LLC
Category: otc | Type: HUMAN OTC DRUG LABEL
Date: 20250217

ACTIVE INGREDIENTS: SALICYLIC ACID 5 mg/1 mL
INACTIVE INGREDIENTS: POLYHYDROXYSTEARIC ACID (2300 MW); BENZALKONIUM CHLORIDE; HEXYLENE GLYCOL; FERROUS OXIDE; COCAMIDOPROPYL PG-DIMONIUM CHLORIDE PHOSPHATE; ALUMINUM OXIDE; ALUMINUM STEARATE; TRIETHOXYCAPRYLYLSILANE; ETHYLENE BRASSYLATE; TITANIUM DIOXIDE; DIMETHICONE/VINYL DIMETHICONE CROSSPOLYMER (SOFT PARTICLE); CAPRYLYL GLYCOL; DISTEARDIMONIUM HECTORITE; CYCLOMETHICONE 5; MAGNESIUM SULFATE, UNSPECIFIED; PHENOXYETHANOL; PEG/PPG-18/18 DIMETHICONE; C12-15 ALKYL LACTATE; CETYL LACTATE; CHAMOMILE; PROPYLENE CARBONATE; POTASSIUM SORBATE; ASCORBYL PALMITATE; TOCOPHEROL; MICA; ISONONYL ISONONANOATE; SILICON DIOXIDE; BIS-PEG/PPG-14/14 DIMETHICONE; VITAMIN A PALMITATE; ALOE VERA LEAF; ALKYL (C12-15) BENZOATE; PROPYLENE GLYCOL; WATER; PANTHENOL

Neutrogena SkinClearing Oil-Free Makeup

Drug Facts

Active ingredient

Salicylic Acid (0.5%)

Purpose

Acne treatment

Use

For the treatment of acne

Warnings

For external use only.

When using this product

Skin irritation and dryness is more likely to occur if you use another topical acne medication at the same time. If irritation occurs, only use one topical acne medication at a time.

Keep out of reach of children. If swallowed, get medical help or contact a Poison Control Center right away.

Directions

• clean the skin thoroughly before applying this product

• cover the entire affected area with a thin layer one to three times daily

• because excessive drying of the skin may occur, start with one application daily, then gradually increase to two or three times daily if needed or as directed by a doctor

• if bothersome dryness or peeling occurs, reduce application to once a day or every other day

Other Information

Store at Room Temperature

Inactive ingredients

Water, Cyclopentasiloxane, Mica, Isononyl Isononanoate, C12-15 Alkyl Benzoate, PEG/PPG-18/18 Dimethicone, Silica, Bis-PEG/PPG-14/14 Dimethicone, Synthetic Wax, C12-15 Alkyl Lactate, Magnesium Sulfate, Panthenol, Polysilicone-11, Cetyl Lactate, Cocamidopropyl PG-Dimonium Chloride Phosphate, Phenoxyethanol, Alumina, Aluminum Stearate, Polyhydroxystearic Acid, Caprylyl Glycol, Disteardimonium Hectorite, Tocopherol, Ethylene Brassylate, Triethoxycaprylylsilane, Potassium Sorbate, Benzalkonium Chloride, Propylene Glycol, Propylene Carbonate, Hexylene Glycol, Chamomilla Recutita (Matricaria) Flower Extract, Ascorbyl Palmitate, Retinyl Palmitate, Aloe Barbadensis Leaf Extract, Iron Oxides, Titanium Dioxide

Questions?

Call toll-free 800-480-4812 or 215-273-8755 (collect) www.neutrogena.com

Distributed by:
Kenvue Brands LLC
Summit, NJ 07901

PRINCIPAL DISPLAY PANEL - 30 mL Bottle Label - Classic Ivory 10

Neutrogena

SkinClearing®

oil-free makeup

MICROCLEAR®

technology

Blemish Treatment

with Salicylic Acid

1 FL OZ (30mL)

PRINCIPAL DISPLAY PANEL - 30 mL Bottle Label - Natural Ivory 20

Neutrogena

SkinClearing®

oil-free makeup

MICROCLEAR®

technology

Blemish Treatment

with Salicylic Acid

1 FL OZ (30mL)

PRINCIPAL DISPLAY PANEL - 30 mL Bottle Label - Buff 30

Neutrogena

SkinClearing®

oil-free makeup

MICROCLEAR®

technology

Blemish Treatment

with Salicylic Acid

1 FL OZ (30mL)

PRINCIPAL DISPLAY PANEL - 30 mL Bottle Label - Nude 40

Neutrogena

SkinClearing®

oil-free makeup

MICROCLEAR®

technology

Blemish Treatment

with Salicylic Acid

1 FL OZ (30mL)

PRINCIPAL DISPLAY PANEL - 30 mL Bottle Label - Soft Beige 50

Neutrogena

SkinClearing®

oil-free makeup

MICROCLEAR®

technology

Blemish Treatment

with Salicylic Acid

1 FL OZ (30mL)

PRINCIPAL DISPLAY PANEL - 30 mL Bottle Label - Natural Beige 60

Neutrogena

SkinClearing®

oil-free makeup

MICROCLEAR®

technology

Blemish Treatment

with Salicylic Acid

1 FL OZ (30mL)

PRINCIPAL DISPLAY PANEL - 30 mL Bottle Label - Fresh Beige 70

Neutrogena

SkinClearing®

oil-free makeup

MICROCLEAR®

technology

Blemish Treatment

with Salicylic Acid

1 FL OZ (30mL)

PRINCIPAL DISPLAY PANEL - 30 mL Bottle Label - Medium Beige 80

Neutrogena

SkinClearing®

oil-free makeup

MICROCLEAR®

technology

Blemish Treatment

with Salicylic Acid

1 FL OZ (30mL)

PRINCIPAL DISPLAY PANEL - 30 mL Bottle Label - Honey 85

Neutrogena

SkinClearing®

oil-free makeup

MICROCLEAR®

technology

Blemish Treatment

with Salicylic Acid

1 FL OZ (30mL)

PRINCIPAL DISPLAY PANEL - 30 mL Bottle Label - Warm Beige 90

Neutrogena

SkinClearing®

oil-free makeup

MICROCLEAR®

technology

Blemish Treatment

with Salicylic Acid

1 FL OZ (30mL)

PRINCIPAL DISPLAY PANEL - 30 mL Bottle Label - Natural Tan 100

Neutrogena

SkinClearing®

oil-free makeup

MICROCLEAR®

technology

Blemish Treatment

with Salicylic Acid

1 FL OZ (30mL)

PRINCIPAL DISPLAY PANEL - 30 mL Bottle Label - Caramel 105

Neutrogena

SkinClearing®

oil-free makeup

MICROCLEAR®

technology

Blemish Treatment

with Salicylic Acid

1 FL OZ (30mL)

PRINCIPAL DISPLAY PANEL - 30 mL Bottle Label - Cocoa 115

Neutrogena

SkinClearing®

oil-free makeup

MICROCLEAR®

technology

Blemish Treatment

with Salicylic Acid

1 FL OZ (30mL)

PRINCIPAL DISPLAY PANEL - 30 mL Bottle Label - Chestnut 135

Neutrogena

SkinClearing®

oil-free makeup

MICROCLEAR®

technology

Blemish Treatment

with Salicylic Acid

1 FL OZ (30mL)